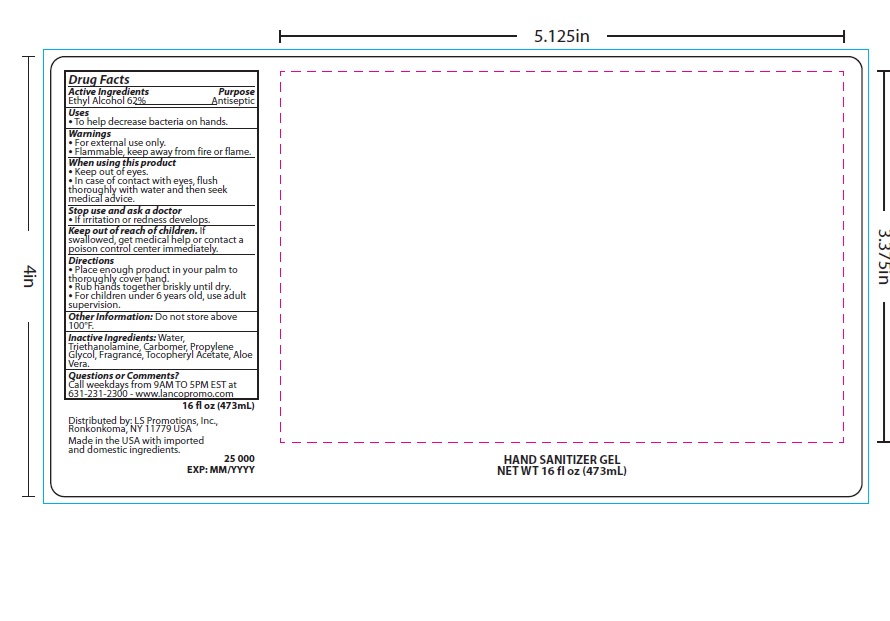 DRUG LABEL: Hand Sanitizer Gel
NDC: 72449-103 | Form: GEL
Manufacturer: LS Promotions Inc.
Category: otc | Type: HUMAN OTC DRUG LABEL
Date: 20250414

ACTIVE INGREDIENTS: ALCOHOL 0.62 mL/1 mL
INACTIVE INGREDIENTS: .ALPHA.-TOCOPHEROL ACETATE, DL-; TRIETHANOLAMINE; FRAGRANCE GREEN APPLE ORC1902709; ALOE VERA WHOLE; PROPYLENE GLYCOL; CARBOMER 1342; WATER

Hand Sanitizer Gel

Drug Facts

Active Ingredients

Ethyl Alcohol 62%

Purpose

Antiseptic

Uses

- To help decrease bacteria on hands.

Warnings

- For external use only
- Flammable, keep away from fire or flame

When using this product

- Keep out of eyes
- In case of contact with eyes, flush thoroughly with water and then seek medical advise

Stop use and ask a doctor

- If irritation or redness develops

Keep out of reach of children

- If swallowed, get medical help or contact a poison control center immediately

Directions

- Place enough product in your palm to thoroughly cover hand.
- Rub hands together briskly until dry.
- For children under 6 years old, use adult supervision.

Other information

- Do not store above 100°F

Inactive Ingredients

Inactive ingredients: water, triethanolamine, carbomer, propylene glycol, fragrance, tocopherol acetate, aloe vera oil.

Questions or Comments?

Call weekdays from 9 AM to 5 PM EST at 631-231-2300

Principal display panel

ABL1211 Hand Sanitizer Gel 16 NDC 72449-103-02